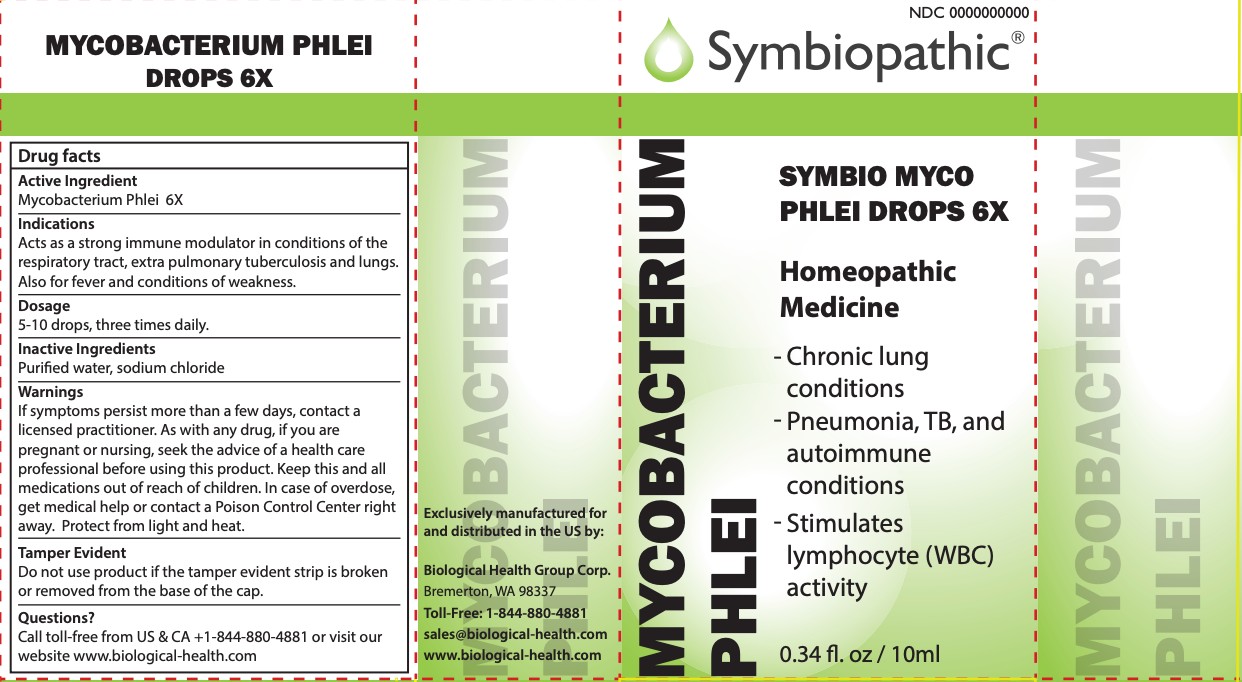 DRUG LABEL: SYMBIOPATHIC
NDC: 69710-255 | Form: LIQUID
Manufacturer: Symbiopathic
Category: homeopathic | Type: HUMAN OTC DRUG LABEL
Date: 20251011

ACTIVE INGREDIENTS: MYCOBACTERIUM PHLEI 6 [hp_X]/1 mL
INACTIVE INGREDIENTS: SODIUM CHLORIDE; WATER

Symbio Myco Phlei Drops 6X

ACTIVE INGREDIENTS:

Mycobacterium Phlei 6X

WARNINGS:

If symptoms persist more than a few days, contact a licensed practitioner. As with any drug, if you are
pregnant or nursing, seek the advice of a health care professional before using this product. Keep this and all medications out of reach of children. In case of overdose, get medical help or contact a Poison Control Center right away. Protect from light and heat.

Tamper Evident
Do not use product if the tamper evident strip is broken
or removed from the base of the cap.

DIRECTIONS:

5-10 drops, three times daily.

INACTIVE INGREDIENTS:

Purified water USP, sodium chloride

KEEP OUT OF REACH OF CHILDREN:In case of overdose, get medical help or call a Poison Control Center right away.

INDICATIONS:

Acts as a strong immune modulator in conditions of the respiratory tract, extra pulmonary tuberculosis and lungs.
Also for fever and conditions of weakness.

QUESTIONS:

Call toll-free from US & CA +1-844-880-4881 or visit our
website www.biological-health.com

PURPOSE:

For internal indications according to traditional homeopathic practice.

OTHER INFORMATION:

Protect from light and heat.

For professional distribution only.

*These statements are based upon traditional homeopathic practice. They have not been reviewed by the Food and Drug Administration.